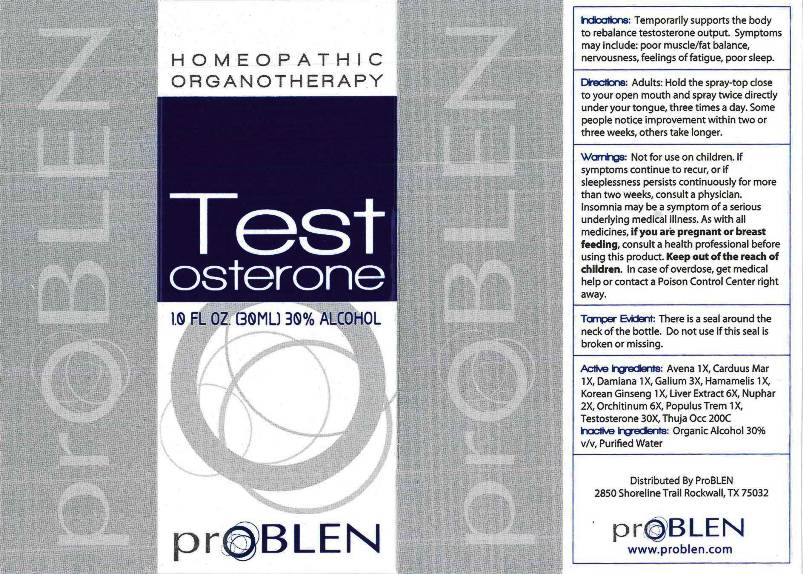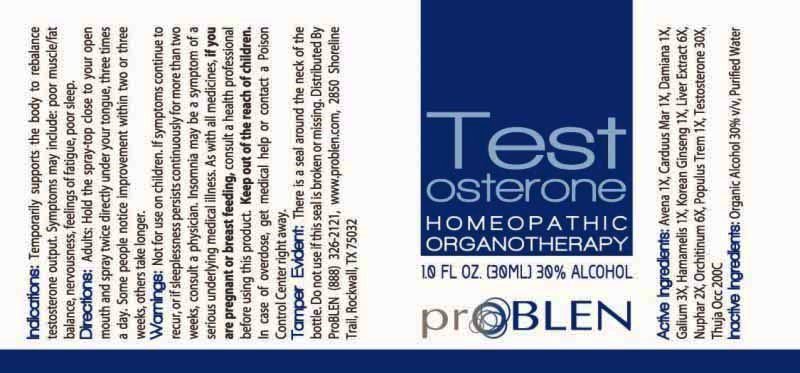 DRUG LABEL: Testosterone
NDC: 43853-0005 | Form: LIQUID
Manufacturer: ProBLEN
Category: homeopathic | Type: HUMAN OTC DRUG LABEL
Date: 20170407

ACTIVE INGREDIENTS: AVENA SATIVA FLOWERING TOP 1 [hp_X]/1 mL; SILYBUM MARIANUM SEED 1 [hp_X]/1 mL; TURNERA DIFFUSA LEAFY TWIG 1 [hp_X]/1 mL; GALIUM APARINE 3 [hp_X]/1 mL; HAMAMELIS VIRGINIANA ROOT BARK/STEM BARK 1 [hp_X]/1 mL; BEEF LIVER 6 [hp_X]/1 mL; ASIAN GINSENG 1 [hp_X]/1 mL; NUPHAR LUTEUM ROOT 2 [hp_X]/1 mL; BOS TAURUS TESTICLE 6 [hp_X]/1 mL; POPULUS TREMULOIDES BARK 1 [hp_X]/1 mL; POPULUS TREMULOIDES LEAF 1 [hp_X]/1 mL; TESTOSTERONE 30 [hp_X]/1 mL; THUJA OCCIDENTALIS LEAF 200 [hp_C]/1 mL
INACTIVE INGREDIENTS: WATER; ALCOHOL

Drug Facts:

ACTIVE INGREDIENTS:

Avena Sativa 1X, Carduus Marianus 1X, Damiana 1X, Galium Aparine 3X, Hamamelis Virginiana 1X, Hepar Bovine 6X, Korean Ginseng 1X, Nuphar Luteum 2X, Orchitinum (Bovine) 6X, Populus Tremuloides 1X, Testosterone 30X, Thuja Occidentalis 200C.

INDICATIONS:

Temporarily supports the body to rebalance testosterone output. Symptoms may include: poor muscle/fat balance, nervousness, feelings of fatigue, poor sleep.

WARNINGS:

Not for use on children. If symptoms continue to recur, or if sleeplessness persists continuously for more than two weeks, consult a physician. Insomnia may be a symptom of a serious underlying medical illness. As with all medicines, if you are pregnant or breast feeding, consult a health professional before using this product. Keep out of the reach of children. In case of overdose, get medical help or contact a Poison Control Center right away.

Tamper Evident: There is a seal around the neck of the bottle. Do not use if this seal is broken or missing.

KEEP OUT OF REACH OF CHILDREN:

Keep out of the reach of children. In case of overdose, get medical help or contact a Poison Control Center right away.

DIRECTIONS:

Adults: Hold the spray-top close to your open mouth and spray twice directly under your tongue, three times a day. Some people notice improvement within two or three weeks, others take longer.

INDICATIONS:

Temporarily supports the body to rebalance testosterone output. Symptoms may include: poor muscle/fat balance, nervousness, feelings of fatigue, poor sleep.

INACTIVE INGREDIENTS:

Purified Water, Organic Ethanol 30%

QUESTIONS:

Distributed By ProBLEN

2850 Shoreline Trail

Rockwall, TX 75032

www.problen.com

PACKAGE LABEL DISPLAY:

Testosterone

HOMEOPATHIC

ORGANOTHERAPY

1.0 FL OZ (30 ML)

proBLEN